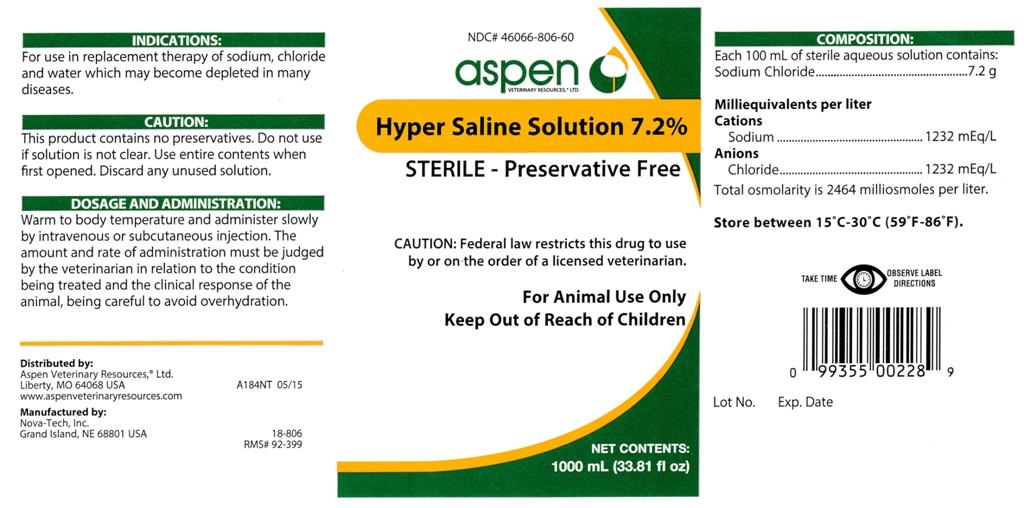 DRUG LABEL: Hypertonic Saline Solution 7.2%
NDC: 46066-806 | Form: INJECTION, SOLUTION
Manufacturer: Aspen Veterinary
Category: animal | Type: PRESCRIPTION ANIMAL DRUG LABEL
Date: 20151110

ACTIVE INGREDIENTS: Sodium Chloride 7.2 g/100 mL

Hypertonic Saline Solution 7.2%

INFORMATION FOR OWNERS/CAREGIVERS

STERILE - Preservative Free

CAUTION:

Federal law restricts this drug to use by or on the order of a licensed veterinarian.

VETERINARY INDICATIONS

For Animal Use Only

Keep Out of Reach of Children

INFORMATION FOR OWNERS/CAREGIVERS

NET CONTENTS:
1000 mL (33.81 fl oz)

INDICATIONS:

For use in replacement therapy of sodium, chloride and water which may become depleted in many diseases.

CAUTION:

This product contains no preservatives. Do not use if solution is not clear. Use entire contents when first opened. Discard any unused solution.

DOSAGE AND ADMINISTRATION:

Warm to body temperature and administer slowly by intravenous or subcutaneous injection. The amount and rate of administration must be judged by the veterinarian in relation to the condition being treated and the clinical response of the animal, being careful to avoid overhydration.

COMPOSITION:

Each 100 mL of sterile aqueous solution contains:
Sodium Chloride..................................7.2 g

Milliequivalents per liter
Cations
Sodium.......................................1232 mEq/L
Anions
Chloride......................................1232 mEq/L

Total osmolarity is 2464 milliosmoles per liter.

STORAGE AND HANDLING

Store between 15 degrees C - 30 degrees C (59 degrees F - 86 degrees F).

INFORMATION FOR OWNERS/CAREGIVERS

Distributed by:
Aspen Veterinary Resources, Ltd.
Liberty, MO 64068 USA A184NT 05/15
www.aspenveterinaryresources.com

Manufactured by:
Nova-Tech, Inc.
Grand Island, NE 68801 USA

18-806
RMS# 92-399

Lot No. Exp. Date

PRECAUTIONS

TAKE TIME OBSERVE LABEL DIRECTIONS